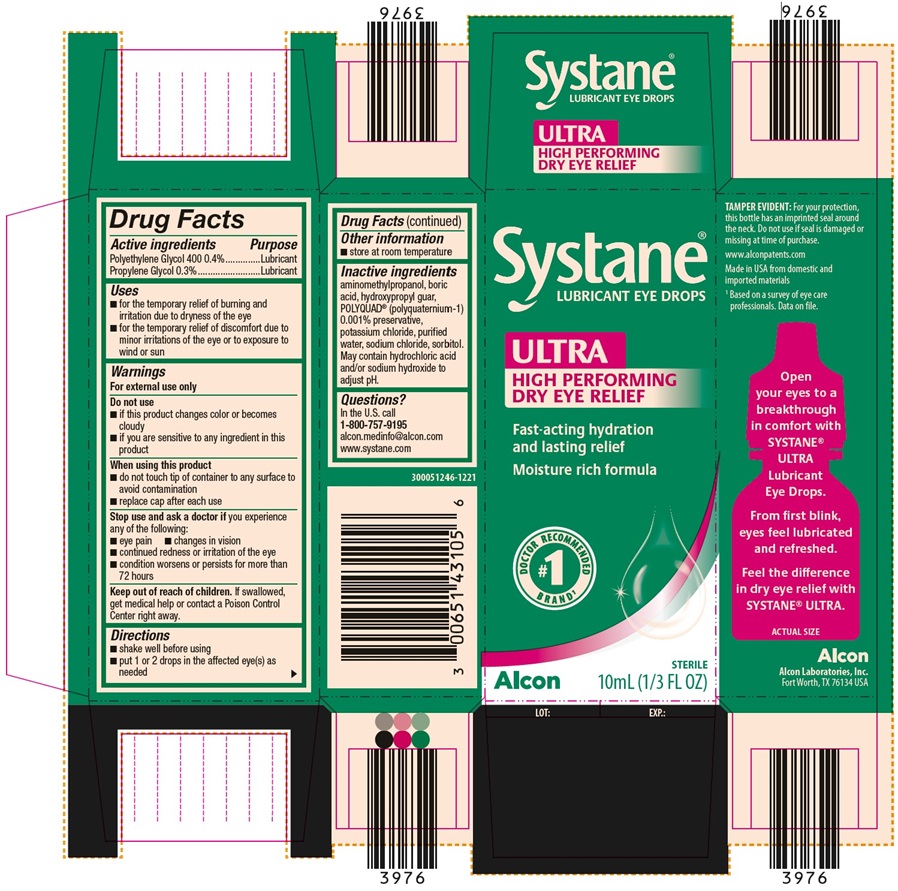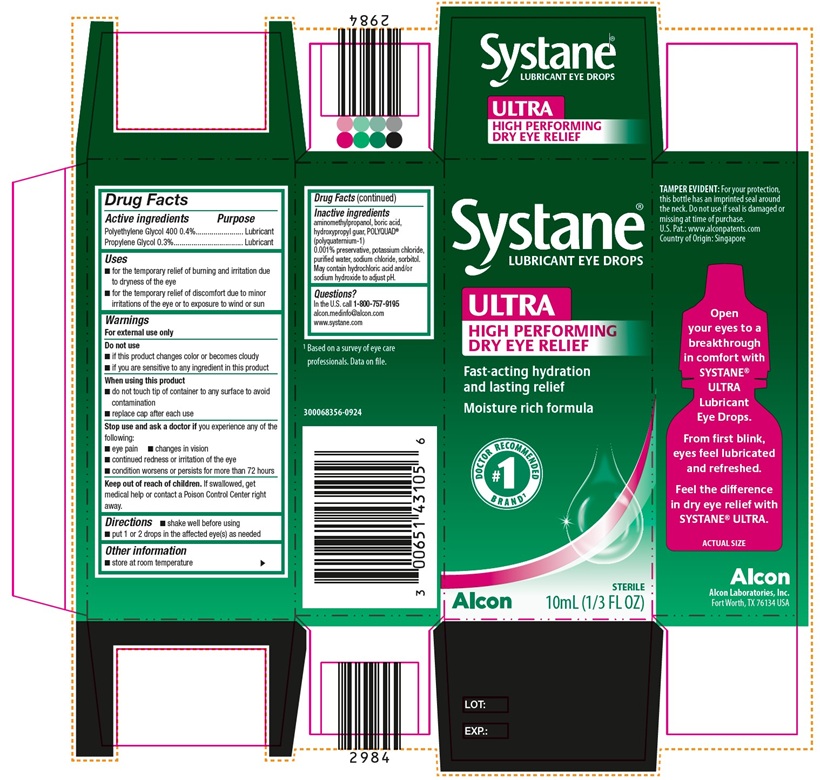 DRUG LABEL: Systane Ultra
NDC: 0065-1431 | Form: SOLUTION/ DROPS
Manufacturer: Alcon Laboratories, Inc.
Category: otc | Type: HUMAN OTC DRUG LABEL
Date: 20250730

ACTIVE INGREDIENTS: Polyethylene Glycol 400 4 mg/1 mL; Propylene Glycol 3 mg/1 mL
INACTIVE INGREDIENTS: Aminomethylpropanol; Boric Acid; Guar Gum; Polidronium Chloride; Potassium Chloride; Water; Sodium Chloride; Sorbitol; Hydrochloric Acid; Sodium Hydroxide

Drug Facts

ACTIVE INGREDIENT

Active Ingredients | Purpose
Polyethylene Glycol 400 0.4% | Lubricant
Propylene Glycol 0.3% | Lubricant

Uses

- for the temporary relief of burning and irritation due to dryness of the eye
- for the temporary relief of discomfort due to minor irritations of the eye or to exposure to wind or sun

Warnings

For external use only

Do not use

- if this product changes color or becomes cloudy
- if you are sensitive to any ingredient in this product

When using this product

- do not touch tip of container to any surface to avoid contamination
- replace cap after each use

Stop use and ask a doctor if

you experience any of the following:

- eye pain
- changes in vision
- continued redness or irritation of the eye
- condition worsens or persists for more than 72 hours

Keep out of reach of children. If swallowed, get medical help or contact a Poison Control Center right away.

Directions

- shake well before using
- put 1 or 2 drops in the affected eye(s) as needed

Other information

- store at room temperature

Inactive ingredients

aminomethylpropanol, boric acid, hydroxypropyl guar, POLYQUAD® (polyquarternium-1) 0.001% preservative, potassium chloride, purified water, sodium chloride, sorbitol. May contain hydrochloric acid and/or sodium hydroxide to adjust pH.

Questions?

In the U.S.
call 1-800-757-9195
alcon.medinfo@alcon.com
www.systane.com

PRINCIPAL DISPLAY PANEL

Systane®
LUBRICANT EYE DROPS
ULTRA
HIGH PERFORMING
DRY EYE RELIEF
Fast-acting hydration
and lasting relief
Moisture rich formula
#1 Doctor Recommended Brand^1
Alcon STERILE
10mL (1/3 FL OZ)
SIDE PANEL:
TAMPER EVIDENT: For your protection, this bottle has an imprinted seal around the neck. Do not use if seal is damaged or missing at time of purchase.
U.S. Pat.: www.alconpatents.com
Country Of Origin: Singapore
Open your eyes to a breakthrough in comfort with Systane® ULTRA Lubricant Eye Drops.
From first blink, eyes feel lubricated and refreshed. Feel the difference in dry eye relief with SYSTANE® ULTRA.
ACTUAL SIZE
Alcon
Alcon Laboratories, Inc.
Fort Worth, TX 76134 USA
^1 Based on a survey of eye care professionals. Data on file.
300068356-0924

Systane®
LUBRICANT EYE DROPS
ULTRA
HIGH PERFORMING
DRY EYE RELIEF
Fast-acting hydration
and lasting relief
Moisture rich formula
#1 Doctor Recommended Brand^1Alcon STERILE
10mL (1/3 FL OZ)
SIDE PANEL:
TAMPER EVIDENT: For your protection, this bottle has an imprinted seal around the neck. Do not use if seal is damaged or missing at time of purchase.
www.alconpatents.com
Made in USA from domestic and imported materials.
Open your eyes to a breakthrough in comfort with Systane® ULTRA Lubricant Eye Drops.
From first blink, eyes feel lubricated and refreshed.
Feel the difference in dry eye relief with SYSTANE® ULTRA.
ACTUAL SIZE
Alcon
Alcon Laboratories, Inc.
Fort Worth, TX 76134 USA
^1Based on a survey of eye care professionals. Data on file.
300051246-1221